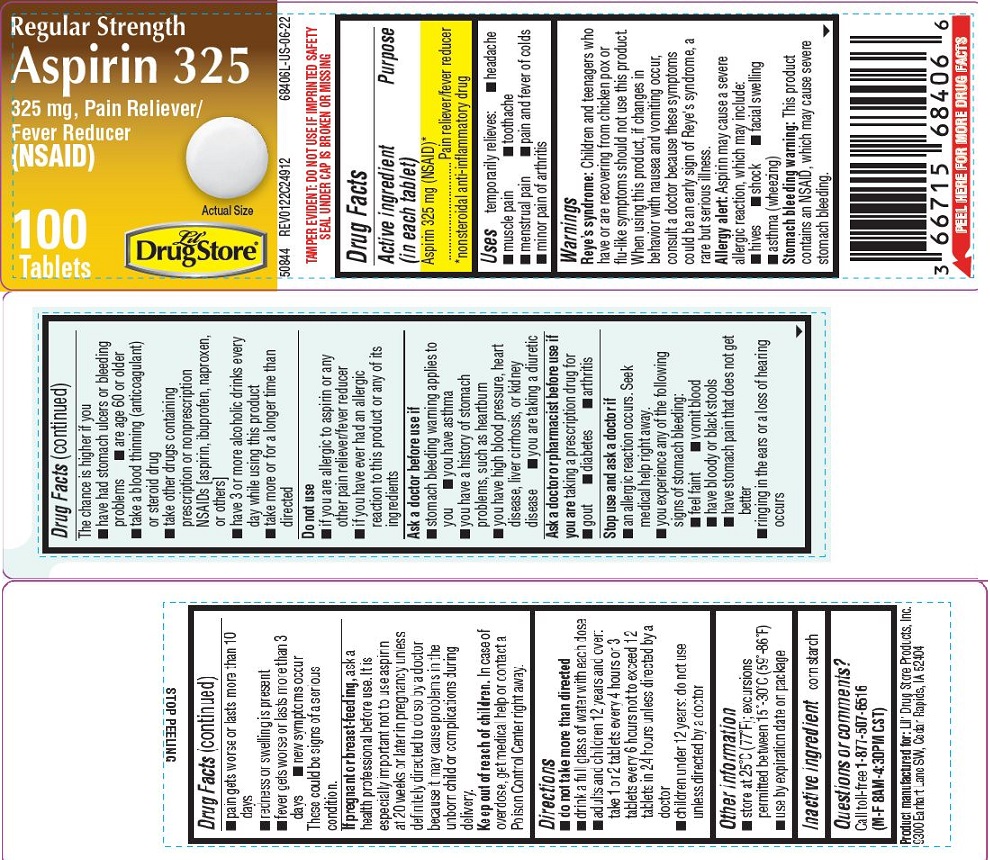 DRUG LABEL: Lil Drug Store Aspirin 325
NDC: 66715-6840 | Form: TABLET
Manufacturer: Lil Drug Store Products, Inc
Category: otc | Type: HUMAN OTC DRUG LABEL
Date: 20231215

ACTIVE INGREDIENTS: ASPIRIN 325 mg/1 1
INACTIVE INGREDIENTS: STARCH, CORN

Lil' Drug Store® Aspirin 325

Drug Facts

Active ingredient (in each tablet)

Aspirin 325 mg (NSAID) [nonsteroidal anti-inflammatory drug]

Purpose

Pain reliever/fever reducer

Uses

temporarily relieves:

- headache
- muscle pain
- menstrual pain
- toothache
- pain and fever of colds
- minor pain of arthritis

Warnings

Reye's syndrome

Children and teenagers who have or are recovering from chicken pox or flu-like symptoms should not use this product. When using this product, if changes in behavior with nausea and vomiting occur, consult a doctor because these symptoms could be an early sign of Reye's syndrome, a rare but serious illness.

Allergy alert

Aspirin may cause a severe allergic reaction, which may include:

- hives
- facial swelling
- shock
- asthma (wheezing)

Stomach bleeding warning

This product contains an NSAID, which may cause severe stomach bleeding. The chance is higher if you:

- are age 60 or older
- have 3 or more alcoholic drinks every day while using this product
- take more or for a longer time than directed
- take other drugs containing prescription or nonprescription NSAIDs [aspirin, ibuprofen,naproxen, or others]
- have had stomach ulcers or bleeding problems
- take a blood thinning (anticoagulant) or steroid drug

Do not use

- if you are allergic to aspirin or any other pain reliever/fever reducer
- if you have ever had an allergic reaction to this product or any of its ingredients

Ask a doctor before use if

- you have a history of stomach problems, such as heartburn
- you have high blood pressure, heart disease, liver cirrhosis, or kidney disease
- you have asthma
- stomach bleeding warning applies to you
- you are taking a diuretic

Ask a doctor or pharmacist before use if you are taking a prescription drug for

- gout
- diabetes
- arthritis

Stop use and ask a doctor if

- you experience any of the following signs of stomach bleeding:
  - vomit blood
  - feel faint
  - have bloody or black stools
  - have stomach pain that does not get better
- an allergic reaction occurs. Seek medical help right away.
- pain gets worse or lasts more than 10 days
- redness or swelling is present
- fever gets worse or lasts more than 3 days
- new symptoms occur
- ringing in the ears or loss of hearing occurs

PREGNANCY OR BREAST FEEDING

If pregnant or breast-feeding, ask a health professional before use. It is especially important not to use aspirin during the last 3 months of pregnancy unless definitely directed to do so by a doctor because it may cause problems in the unborn child or complications during delivery.

Keep out of reach of children. In case of overdose, get medical help or contact a Poison Control Center (1-800-222-1222) right away.

Directions

- drink a full glass of water with each dose
- adults and children 12 years and over: take 1 or 2 tablets every 4 hours or 3 tablets every 6 hours, not to exceed 12 tablets in 24 hours
- children under 12 years: ask a doctor

Other information

- use by expiration date on package
- store at 25°C (77°F); excursions permitted between 15°-30°C (59°-86°F)

Inactive ingredient

corn starch

Questions or comments?

Call toll-free 1-877-507-6516 (M-F 8AM-4:30PM CST)

PRINCIPAL DISPLAY PANEL - 325 mg Tablet Bottle Label

Regular Strength

Aspirin 325

325 mg, Pain Reliever/
Fever Reducer (NSAID)

100
Tablets

Lil'
Drug Store®